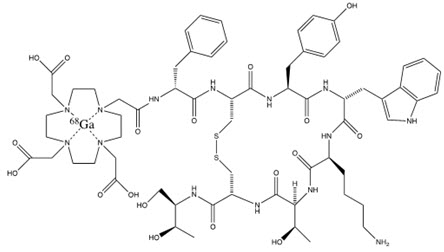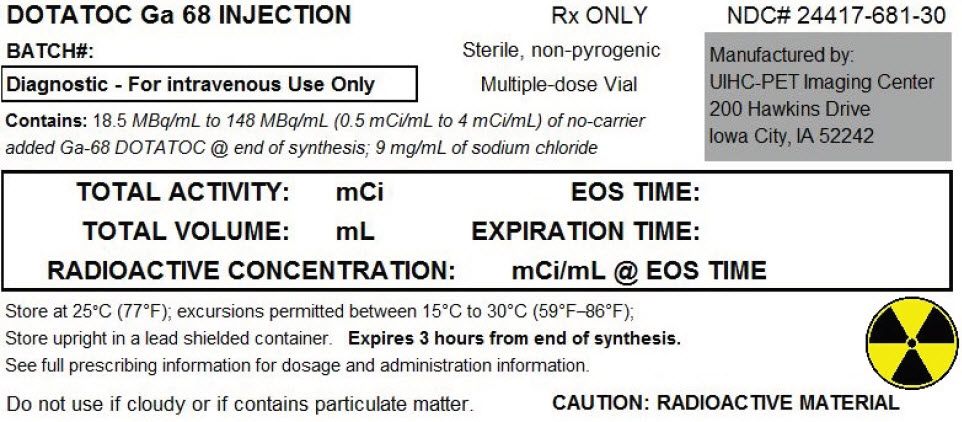 DRUG LABEL: Ga-68-DOTATOC
NDC: 24417-681 | Form: INJECTION, SOLUTION
Manufacturer: UIHC – P E T Imaging Center
Category: prescription | Type: HUMAN PRESCRIPTION DRUG LABEL
Date: 20211208

ACTIVE INGREDIENTS: EDOTREOTIDE GALLIUM GA-68 4 mCi/1 mL
INACTIVE INGREDIENTS: ALCOHOL; sodium chloride

HIGHLIGHTS OF PRESCRIBING INFORMATION

These highlights do not include all the information needed to use Ga 68 DOTATOC INJECTION safely and effectively. See full prescribing information for Ga 68 DOTATOC INJECTION.
Ga 68 DOTATOC Injection, for intravenous use
Initial U.S. Approval: 2019

RECENT MAJOR CHANGES

Warnings and Precautions (5.2) | 12/2021

1 INDICATIONS AND USAGE

Ga 68 DOTATOC Injection is a radioactive diagnostic agent indicated for use with positron emission tomography (PET) for localization of somatostatin receptor positive neuroendocrine tumors (NETs) in adult and pediatric patients. (1)

2 DOSAGE AND ADMINISTRATION

- Recommended dose for adults is 148 MBq (4 mCi) as a bolus intravenous injection (2.2)
- Recommended dose for pediatric patients is 1.59 MBq/kg (0.043 mCi/kg) with a range of 11.1 MBq (0.3 mCi) to 111 MBq (3 mCi), as a bolus intravenous injection (2.2)
- Initiate imaging 55 to 90 minutes after drug administration (2.4)
- See full prescribing information for additional preparation, administration, imaging and radiation dosimetry information (2)

3 DOSAGE FORMS AND STRENGTHS

Injection: 18.5 MBq/mL to 148 MBq/mL (0.5 mCi/mL to 4 mCi/mL) of Ga 68 DOTATOC Injection in a multiple-dose glass vial (3)

4 CONTRAINDICATIONS

None (4)

5 WARNINGS AND PRECAUTIONS

- Radiation Risk: Ensure safe handling and preparation procedures to protect patients and health care workers from unintentional radiation exposure Advise patients to hydrate before and after administration and to void frequently after administration (2.1, 2.3, 5.1)
- Hypersensitivity Reactions: Most reported reactions were rash and pruritus and reversible either spontaneously or with routine symptomatic management. (5.2)
- Risk for Image Misinterpretation: Uptake of Ga 68 DOTATOC injection can be seen in a variety of tumor types that contain somatostatin receptors, and in other pathologic conditions, and as a normal physiologic variant (e.g. uncinate process of the pancreas) (5.3)

6 ADVERSE REACTIONS

Reported adverse reactions include: Nausea, pruritis, and flushing.

To report SUSPECTED ADVERSE REACTIONS, contact the UIHC – P E T Imaging Center at 1-319-356-1092 or FDA at 1-800-FDA-1088 or www.fda.gov/medwatch (6)

7 DRUG INTERACTIONS

Somatostatin Analogs: Somatostatin analogs competitively bind to the same somatostatin receptors as Ga 68 DOTATOC Injection and may affect imaging –Discontinue short-acting somatostatin analogs 24 hours before imaging with Ga 68 DOTATOC and image just prior to dosing with long-acting somatostatin analogs (2.3, 7)

8 USE IN SPECIFIC POPULATIONS

Lactation: Breast milk should be pumped and discarded for 8 hours after administration (8.2)

FULL PRESCRIBING INFORMATION

1 INDICATIONS AND USAGE

Ga 68 DOTATOC Injection is indicated for use with positron emission tomography (PET) for the localization of somatostatin receptor positive neuroendocrine tumors (NETs) in adult and pediatric patients.

2 DOSAGE AND ADMINISTRATION

2.1 Radiation Safety – Drug Handling

Handle Ga 68 DOTATOC Injection with appropriate safety measures to minimize radiation exposure [see Warnings and Precautions (5.1)]. Use waterproof gloves, effective radiation shielding and appropriate safety measures when preparing and handling Ga 68 DOTATOC Injection.

Radiopharmaceuticals should be used by or under the control of physicians who are qualified by specific training and experience in the safe use and handling of radionuclides, and whose experience and training have been approved by the appropriate governmental agency authorized to license the use of radionuclides.

2.2 Recommended Dosage and Administration Instructions

Recommended Dosage

In adults, the recommended amount of radioactivity to be administered for PET imaging is 4 mCi (148 MBq) with a range of 3 mCi to 5 mCi (111 MBq to 185 MBq) administered as an intravenous injection with an injection rate of approximately 10 seconds per mL.

In pediatric patients, the recommended amount of radioactivity to be administered for PET imaging is 0.043 mCi/kg of body weight (1.59 MBq/kg) with a range of 0.3 mCi (11.1 MBq) to 3 mCi (111 MBq) as an intravenous injection with an injection rate of approximately 10 seconds per mL.

Administration

- Use Ga 68 DOTATOC Injection within 3 hours of calibration time.
- Use aseptic technique and radiation shielding when withdrawing and administering Ga 68 DOTATOC Injection.
- Inspect Ga 68 DOTATOC Injection visually for particulate matter and discoloration before administration. Do not use the drug if the solution contains particulate matter or is discolored.
- Calculate the necessary volume to administer based on measured activity, volume, calibration time, and date.
- Measure the patient dose immediately prior to administration in a dose calibrator.
- After injection of Ga 68 DOTATOC Injection, administer an intravenous flush of sodium chloride injection, 0.9% to ensure full delivery of the dose.
- Dispose of any unused drug in a safe manner in compliance with applicable regulations.

2.3 Use with Somatostatin Analogs and Patient Hydration

Somatostatin Analogs

Somatostatin analogs bind to the same somatostatin receptors as Ga 68 DOTATOC

- Discontinue short-acting somatostatin analogs 24 hours before imaging with Ga 68 DOTATOC Injection.
- Image patients with Ga 68 DOTATOC Injection just prior to dosing with long-acting analogs of somatostatin [see Drug Interactions (7)].

Patient Hydration

Instruct patients to drink water to ensure adequate hydration prior to administration of Ga 68 DOTATOC Injection and to continue to drink and void frequently during the first hours following administration to reduce radiation exposure [see Warnings and Precautions (5.1)].

2.4 Image Acquisition

For Ga 68 DOTATOC PET imaging, a whole-body acquisition from the skull vertex to mid-thigh is recommended. Image acquisition can begin at 60 minutes (range 55 to 90 minutes) after the intravenous administration of the Ga 68 DOTATOC Injection. Adapt Ga 68 DOTATOC Injection uptake time and scan duration according to the equipment used, and the patient and tumor characteristics, to obtain the optimal image quality.

2.5 Image Interpretation

Ga 68 DOTATOC binds to somatostatin receptors. Based upon the intensity of the signals, PET images obtained using Ga 68 DOTATOC Injection indicate the presence and density of somatostatin receptors in tissues, .Uptake can also be seen in a variety of non-NET tumors that contain somatostatin receptors or as a normal physiologic variant [see Warnings and Precautions (5.2)]. NET tumors that do not bear somatostatin receptors will not be visualized.

2.6 Radiation Dosimetry

Estimated radiation absorbed doses per injected activity for organs and tissues of adult patients following an intravenous bolus of Ga 68 DOTATOC Injection are shown in Table 1. Estimated radiation effective doses per injected activity for adult and pediatric patients following an intravenous bolus administration of Ga 68 DOTATOC Injection are shown in Table 2.

Table 1: Estimated Radiation Absorbed Dose per Injected Activity in Selected Organs with Ga 68 DOTATOC
Site | Absorbed Dose (mGy/MBq)
Urinary bladder wall | 0.119 ± 0.058
Spleen | 0.108 ± 0.065
Kidney | 0.082 ± 0.020
Adrenal gland | 0.077 ± 0.028
Liver | 0.041 ± 0.014
Red marrow | 0.016 ± 0.003
Gallbladder wall | 0.015 ± 0.001
Total body | 0.014 ± 0.002
Lungs | 0.007 ± 0.001
Effective dose (mSv/MBq) | 0.021 ± 0.003

The effective radiation dose resulting from the administration of 148 MBq (4 mCi) to an adult weighing 75 kg, is about 3.11 mSv. For an administered activity of 148 MBq (4 mCi) the typical radiation dose to the critical organs, which are the urinary bladder wall, the spleen and the kidneys/adrenals, are about 18 mSv, 16 mSv and 12 mSv, respectively. Because the spleen has one of the highest physiological uptakes, higher uptake and radiation dose to other organs or pathologic tissues may occur in patients with splenectomy.

Table 2: Estimated Radiation Effective Dose per Injected Activity after a Ga-68 DOTATOC Injection
Age | Model Weight (kg) | Effective Dose per Injection Activity (mSv/MBq)
Adult | 73.7 | 0.019
15 years | 56.8 | 0.026
10 years | 33.2 | 0.041
5 years | 19.8 | 0.066
1 year | 9.7 | 0.13
Newborn | 3.6 | 0.36

3 DOSAGE FORMS AND STRENGTHS

Injection: Gallium Ga 68 DOTATOC Injection is a clear, colorless solution in a 30 mL multiple-dose vial containing 18.5 MBq/mL to 148 MBq/mL (0.5 mCi/mL to 4 mCi/mL) of Ga 68 DOTATOC Injection at calibration date and time.

4 CONTRAINDICATIONS

None

5 WARNINGS AND PRECAUTIONS

5.1 Radiation Risk

Ga 68 DOTATOC Injection contributes to a patient's overall long-term cumulative radiation exposure. Long-term cumulative radiation exposure is associated with an increased risk of cancer. Ensure safe handling and preparation procedures to protect patients and health care workers from unintentional radiation exposure. Advise patients to hydrate before and after administration and to void frequently after administration [see Dosage and Administration (2.1, 2.3)].

5.2 Hypersensitivity Reactions

Hypersensitivity reactions following administration of somatostatin receptor imaging agents predominantly consisted of cutaneous reactions such as rash and pruritus. Reactions reversed either spontaneously or with routine symptomatic management. Less frequently hypersensitivity reactions included angioedema or cases with features of anaphylaxis.

5.3 Risk for Image Misinterpretation

The uptake of Ga 68 DOTATOC Injection reflects the level of somatostatin receptor density in NETs, however, uptake can also be seen in a variety of other tumors that also express somatostatin receptors. Increased uptake might also be seen in other non-cancerous pathologic conditions that express somatostatin receptors including thyroid disease or in subacute inflammation, or might occur as a normal physiologic variant (e.g. uncinate process of the pancreas) [see Dosage and Administration (2.5)].

A negative scan after the administration of Ga 68 DOTATOC Injection in patients who do not have a history of NET disease does not rule out disease [see Clinical Studies (14)].

6 ADVERSE REACTIONS

The following clinically significant adverse reactions are described elsewhere in the labeling:

- Hypersensitivity reactions

6.1 Clinical Trial Experience

Because clinical trials are conducted under widely varying conditions, adverse reaction rates observed in the clinical trials of a drug cannot be directly compared to rates in the clinical trials of another drug and may not reflect the rates observed in practice.

The safety of Ga-68 DOTATOC injection was evaluated in 334 patients in clinical trials of patients receiving a single dose of Ga-68 DOTATOC injection for imaging known or suspected NET.

The following adverse reactions occurred at a rate of < 2%:
Gastrointestinal Disorders: nausea

The following adverse reactions occurred at a rate of a < 1%
Skin and Subcutaneous Tissue Disorders: pruritus
Vascular Disorders: flushing

6.2 Postmarketing Experience

The following adverse reactions have been identified during postapproval use of other somatostatin receptor imaging agents. Because these reactions are reported voluntarily from a population of uncertain size, it is not always possible to reliably estimate their frequency or establish a causal relationship to the drug.

Immune System Disorders: Hypersensitivity reactions, predominantly rash, pruritus, less frequently angioedema or features of anaphylaxis

7 DRUG INTERACTIONS

Non-radioactive somatostatin analogs bind to the same somatostatin receptors as Ga 68 DOTATOC Injection. Image patients with Ga 68 DOTATOC Injection just prior to dosing with long-acting analogs of somatostatin. Short-acting analogs of somatostatin can be used up to 24 hours before imaging with Ga 68 DOTATOC Injection [see Dosage and Administration (2.3)].

8 USE IN SPECIFIC POPULATIONS

8.1 Pregnancy

Risk Summary

There are no available data on the use of Ga 68 DOTATOC Injection in pregnant women to identify a risk of major birth defects, miscarriage or adverse maternal or fetal outcomes. Animal reproduction studies have not been conducted with Ga 68 DOTATOC. However, all radiopharmaceuticals, including Ga 68 DOTATOC Injection have the potential to cause fetal harm depending on the fetal stage of development and the magnitude of the radiation dose. If considering Ga 68 DOTATOC Injection administration to a pregnant woman, inform the patient of the potential for adverse pregnancy outcomes based on the radiation dose from Ga 68 DOTATOC Injection and the gestational timing of exposure.

The estimated background risk of major birth defects and miscarriage for the indicated population is unknown. All pregnancies have a background risk of birth defect, loss, or other adverse outcomes. In the U.S general population, the estimated background risks of major birth defects and miscarriage in clinically recognized pregnancies are 2-4% and 15-20%, respectively.

8.2 Lactation

Risk Summary

There is no information on the presence of Ga 68 DOTATOC in human milk, the effect on the breastfed infant, or the effect on milk production. The developmental and health benefits of breastfeeding should be considered along with the mother's clinical need for Ga 68 DOTATOC Injection and any potential adverse effects on the breastfed child from Ga 68 DOTATOC Injection or from the underlying maternal condition.

Clinical Considerations

To decrease exposure to the breastfed infant, advise a lactating woman to interrupt breastfeeding and pump and discard breast milk for 8 hours after Ga 68 DOTATOC Injection administration.

8.4 Pediatric Use

The safety and efficacy of Ga 68 DOTATOC Injection have been established in pediatric patients with neuroendocrine tumors. Efficacy is based on data from 14 patients in Study A and B demonstrating the ability of Ga 68 DOTATOC to image NETs [see Clinical Studies (14)]. The safety profile of Ga 68 DOTATOC Injection is similar in adult and pediatric patients with somatostatin receptor positive tumors. The recommended Ga 68 DOTATOC injected dose in pediatric patients is weight based [see Dosage and Administration (2.2)].

8.5 Geriatric Use

Clinical studies of Ga 68 DOTATOC did not include sufficient numbers of subjects aged 65 and over to determine whether they respond differently from younger subjects. Other reported clinical experience has not identified differences in responses between the elderly and younger patients. In general, dose selection for an elderly patient should be cautious, usually starting at the low end of the dosing range, reflecting the greater frequency of decreased hepatic, renal, or cardiac function, and of concomitant disease or other drug therapy.

10 OVERDOSAGE

In the event of a radiation overdose, reduce the absorbed dose to the patient by increasing the elimination of the radionuclide from the body by reinforced hydration, frequent bladder voiding, and diuretics, if needed. If possible, perform an estimate of the radioactive dose given to the patient.

11 DESCRIPTION

11.1 Chemical Characteristics

Ga 68 DOTATOC Injection is a radioactive diagnostic agent for intravenous administration. It contains 3.6 mcg/mL (DOTA-0-Phe1-Tyr3) octreotide, 18.5 MBq/mL to 148 MBq/mL (0.5 mCi to 4 mCi/mL) of Ga 68 DOTATOC at calibration time, and ethanol (10% v/v) in sodium chloride (9 mg/mL) solution (approximately 14 mL volume). Ga 68 DOTATOC Injection is a sterile, pyrogen free, clear, colorless, buffered solution, with a pH between 4 to 8.

Ga 68 DOTATOC, also known as Gallium-68 (DOTA0-Phe1-Tyr3) octreotide, is a cyclic 8 amino acid peptide with a covalently bound chelator (DOTA). The peptide has the amino acid sequence: H-D-Phe-Cys-Tyr-D-Trp-Lys-Thr-Cys-Thr-OH, and contains one disulfide bond. Ga 68 DOTATOC has a molecular weight of 1489.65 g/mol and its chemical structure is shown in Figure 1.

Figure 1: Chemical Structure of Ga 68 DOTATOC

Gallium-68 labeled 2-[4-[2-[[(2R)-1-[[(4R,7S,10S,13R,16S,19R)-10-(4-aminobutyl)-4-[[(2R,3R)-1,3-dihydroxybutan-2-yl]carbamoyl]-7-[(1R)-1-hydroxyethyl]-16-[(4-hydroxyphenyl)methyl]-13-(1H-indol-3-ylmethyl)-6,9,12,15,18-pentaoxo-1,2-dithia-5,8,11,14,17-pentazacycloicos-19-yl]amino]-1-oxo-3-phenylpropan-2-yl]amino]-2-oxoethyl]-7,10-bis(carboxymethyl)-1,4,7,10-tetrazacyclododec-1-yl]acetic acid.

11.2 Physical Characteristics

Table 3 and Table 4 display the principal radiation emission data and physical decay of Ga 68.

Gallium-68 (Ga 68) decays with a half-life of 68 minutes to stable Zn 68:

- 89% through positron emission with a mean energy of 836 keV followed by emission of two 511 keV annihilation photons (178%),
- 10% through orbital electron capture (with associated X-ray or Auger emissions), and
- 3% through 13 gamma transitions from 5 excited levels of the daughter Zn 68 nucleus. The most probable prompt gamma emission is a 1088 keV gamma with a 3.2% per decay probability.

Table 3: Principal Radiation Emission Data (>1%)
Radiation/Emission | % Disintegration | Mean Energy (MeV)
beta+ | 88% | 0.8360
beta+ | 1.1% | 0.3526
gamma | 178% | 0.5110
gamma | 3% | 1.0770
X-ray | 2.8% | 0.0086
X-ray | 1.4% | 0.0086

Table 4: Physical Decay Chart for Gallium Ga-68
Minutes | Fraction Remaining
0 | 1.000
15 | 0.858
30 | 0.736
60 | 0.541
90 | 0.398
120 | 0.293
180 | 0.158
360 | 0.025

11.3 External Radiation

Gamma constant: 1.8 × 10^-4 mSv/hr per MBq at 1 meter [0.67 mrem/hr per mCi at 1 meter] Table 5 displays the radiation attenuation by lead shielding of Ga 68.

Table 5: Radiation Attenuation of 511 keV Photons by Lead (Pb) Shielding
Shield Thickness (Pb) mm | Coefficient of Attenuation
6 | 0.5
12 | 0.25
17 | 0.1
34 | 0.01
51 | 0.001

12 CLINICAL PHARMACOLOGY

12.1 Mechanism of Action

Ga 68 DOTATOC binds to somatostatin receptors, with highest affinity (Ki = 2.5± 0.5 nanomolar) for subtype 2 receptors (sstr2). Ga 68 DOTATOC binds to cells that express somatostatin receptors including malignant neuroendocrine cells, which overexpress sstr2 receptors. Gallium 68 is a β+ emitting radionuclide with associated 511 keV annihilation photons that allow positron emission tomography (PET) imaging.

12.2 Pharmacodynamics

The relationship between Ga 68 DOTATOC plasma concentrations and successful imaging was not explored in clinical trials.

12.3 Pharmacokinetics

Distribution

Ga 68 DOTATOC distributes to all sstr2-expressing organs such as pituitary, thyroid, spleen, adrenals, kidney, pancreas, prostate, liver, and salivary glands. Uptake in the lung and lymph nodes are lower as compared to other sstr-2 expressing organs.

Elimination

Radiotracer elimination is exclusively via urine. Approximately 16% of the injected dose is excreted in urine in the first two to four hours post-injection.

14 CLINICAL STUDIES

The safety and efficacy of Ga-68 DOTATOC Injection were established in two single-center, open-label studies (Study A and Study B) in which 282 patients with known or suspected SSTR-positive NETs received a single dose of Ga-68 DOTATOC. A total of 238 of the 282 patients (84%) had a history of neoplasm at the time of Ga-68 DOTATOC imaging. Among the 282 patients, 59% were female and 95% white; the mean age was 54 years (range from 4 to 82 years).

The Ga-68 DOTATOC images were rated by two independent readers blinded to clinical information as either positive or negative for NET within each patient. The imaging results were compared to a composite reference consisting of histopathology and imaging (MR, CT, or In-111 pentetreotide imaging) acquired within 1 year of the Ga-68 DOTATOC imaging, as well as chromogranin A and pancreastatin levels. The proportion of patients positive for NET per composite reference who were identified as positive by the Ga-68 DOTATOC image was used to quantify positive percent agreement. The proportion of patients without NET per composite reference who were identified as negative by the Ga-68 DOTATOC image was used to quantify negative percent agreement.

Study A (NCT: 01619865) included 220 subjects with known or suspected SSTR positive tumors referred for diagnosis or evaluation of disease extension before or after treatment. A total of 178 of the 220 patients (81%) had a history of neoplasm at the time of Ga-68 DOTATOC imaging. In 177 of the 220 patients, sufficient data to establish NET status per composite reference was available for efficacy evaluation. Table 6 shows the performance of Ga-68 DOTATOC in the detection of NETs for Study A.

Table 6: Study A. Performance of Ga-68 DOTATOC in the detection of NET by reader
N = 177 | NET status as identified by reader | Reference
N = 177 | NET status as identified by reader | Positive | Negative
Reader 1 | Positive | 121 | 5
Reader 1 | Negative | 12 | 39
Reader 1
Reader 1 | Agreement (%) [Percent reader agreement with reference;] (95% CI) [Exact method] | 91 (85, 95) | 89 (75, 96)
Reader 2 | Positive | 120 | 6
Reader 2 | Negative | 13 | 38
Reader 2
Reader 2 | Agreement (%) (95% CI) | 90 (84, 95) | 86 (73, 95)
N: number of patients, CI: confidence interval,

Study B (NCT: 01869725) included 62 patients with histologically positive NET or other SSTR positive tumor referred for evaluation of disease before or after treatment. In 59 of the 62 patients, sufficient data to establish NET status per composite reference was available for efficacy evaluation. The estimated positive and negative percent agreements were 92% and 75% for reader 1 and 90% and 75% for reader 2, respectively.

16 HOW SUPPLIED/STORAGE AND HANDLING

Ga 68 DOTATOC Injection is supplied in a multiple-dose, capped 30 mL glass vial containing 18.5 MBq/mL to 148 MBq/mL (0.5 mCi/mL to 4 mCi/mL) of Ga 68 DOTATOC at calibration time in approximately 14 mL of solution (NDC 24417-681-30).

STORAGE AND HANDLING

Store Ga 68 DOTATOC Injection upright in a lead shielded container at 25°C (77°F); excursions permitted to 15°C to 30°C (59°F to 86°F).

Receipt, transfer, handling, possession or use of this product is subject to the radioactive material regulations and licensing requirements of the U.S. Nuclear Regulatory Commission, Agreement States or Licensing States as appropriate. Store and dispose of Ga 68 DOTATOC Injection in accordance with the regulations and a general license, or its equivalent, of an Agreement State or a Licensing State.

17 PATIENT COUNSELING INFORMATION

Radiation Risk

Advise patients to drink water to ensure adequate hydration prior to their PET study and recommend they drink and urinate as often as possible during the first hours following the administration of Ga 68 DOTATOC Injection, in order to reduce radiation exposure [see Dosage and Administration (2.3) and Warnings and Precautions (5.1)].

Lactation

Advise a lactating woman to interrupt breastfeeding and pump and discard breast milk for 8 hours after Ga 68 DOTATOC Injection administration in order to minimize radiation exposure to a breastfed infant [see Use in Specific Populations (8.2)].

Manufactured and Distributed by:
UIHC – P E T Imaging Center
0911Z JPP
200 Hawkins Drive
Iowa City, IA 52242

PRINCIPAL DISPLAY PANEL - 14 mL Vial Label

DOTATOC Ga 68 INJECTION

BATCH#
Diagnostic - For intravenous Use Only
Contains: 18.5 MBq/mL to 148 MBq/mL (0.5 mCi/mL to 4 mCi/mL) of no-carrier
added Ga-68 DOTATOC @ end of synthesis; 9 mg/mL of sodium chloride

Rx ONLY

Sterile, non-pyrogenic

Multiple-dose Vial

NDC# 24417-681-30

Manufactured by:
UIHC-PET Imaging Center
200 Hawkins Drive
Iowa City, IA 52242

TOTAL ACTIVITY: mCi
TOTAL VOLUME: mL
RADIOACTIVE CONCENTRATION: mCi/mL @ EOS TIME
EOS TIME:
EXPIRATION TIME:

Store at 25°C (77°F); excursions permitted between 15°C to 30°C (59°F–86°F);
Store upright in a lead shielded container. Expires 3 hours from end of synthesis.
See full prescribing information for dosage and administration information.

Do not use if cloudy or if contains particulate matter.
CAUTION: RADIOACTIVE MATERIAL